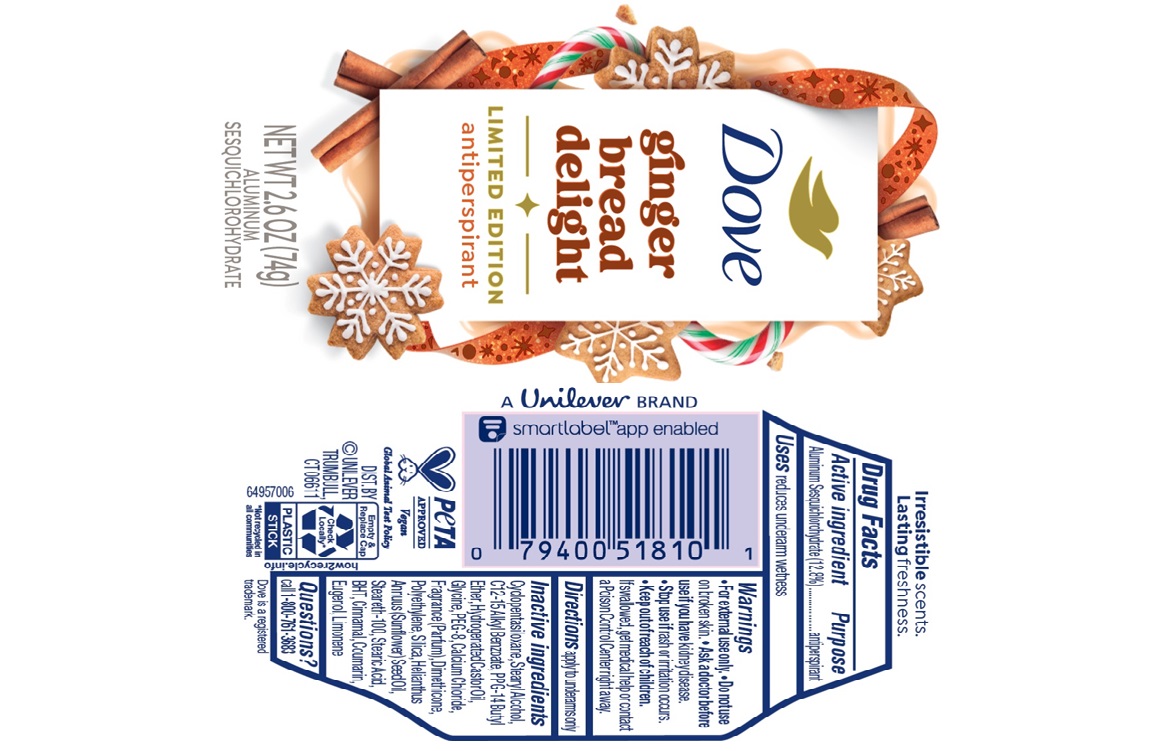 DRUG LABEL: Dove
NDC: 64942-2377 | Form: STICK
Manufacturer: Conopco d/b/a Unilever
Category: otc | Type: HUMAN OTC DRUG LABEL
Date: 20250715

ACTIVE INGREDIENTS: ALUMINUM SESQUICHLOROHYDRATE 12.8 g/100 g
INACTIVE INGREDIENTS: STEARIC ACID; LIMONENE, (+)-; CALCIUM CHLORIDE; POLYETHYLENE; CYCLOPENTASILOXANE; STEARYL ALCOHOL; C12-15 ALKYL BENZOATE; HYDROGENATED CASTOR OIL; EUGENOL; PPG-14 BUTYL ETHER; GLYCINE; PEG-8; SILICA; BHT; CINNAMAL; DIMETHICONE; STEARETH-100; HELIANTHUS ANNUUS (SUNFLOWER) SEED OIL; COUMARIN

Dove Ginger Bread Delight Limited Edition Antiperspirant

DESCRIPTION

Dove Ginger Bread Delight Limited Edition Antiperspirant

ACTIVE INGREDIENT

Aluminum Sesquichlorohydrate 12.8%

PURPOSE

Antiperspirant

INDICATIONS AND USAGE

apply to underarms only

WARNINGS

For external use only.
• Do not use on broken skin.• Ask a doctor before
use if you have kidney disease. • Stop use if rash or irritation occurs.

Keep out of reach of children. If swallowed,get medical help or contact a Poison Control Center right away

DOSAGE AND ADMINISTRATION

apply to underarms only

INACTIVE INGREDIENT

Cyclopentasiloxane, Stearyl Alcohol, C12-15 Alkyl Benzoate,PPG-14 Butyl Ether, Hydrogenated Castor Oil, Glycine, PEG-8, Calcium Chloride, Fragrance (Parfum), Dimethicone, Polyethylene, Silica, Helianthus Annuus (Sunflower) Seed Oil, Steareth-100, Stearic Acid, BHT, Cinnamal, Coumarin, Eugenol, Limonene

QUESTIONS

call 1-800-761-3683